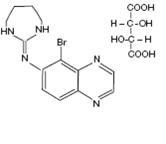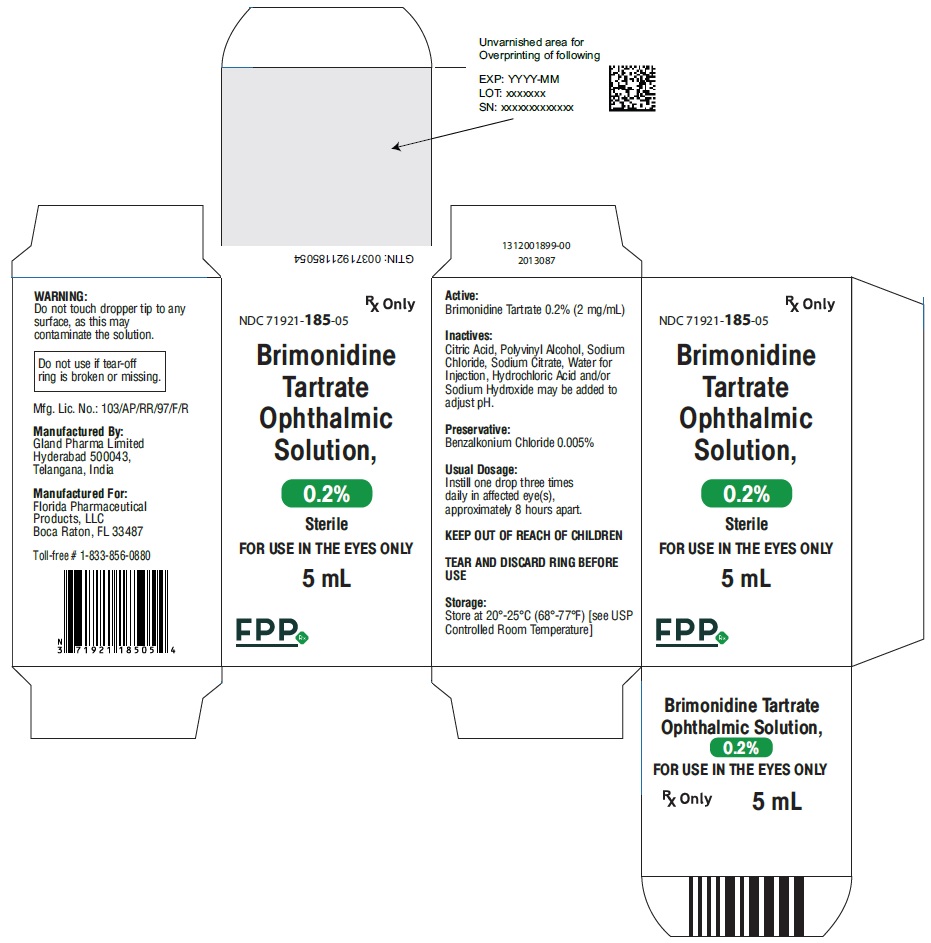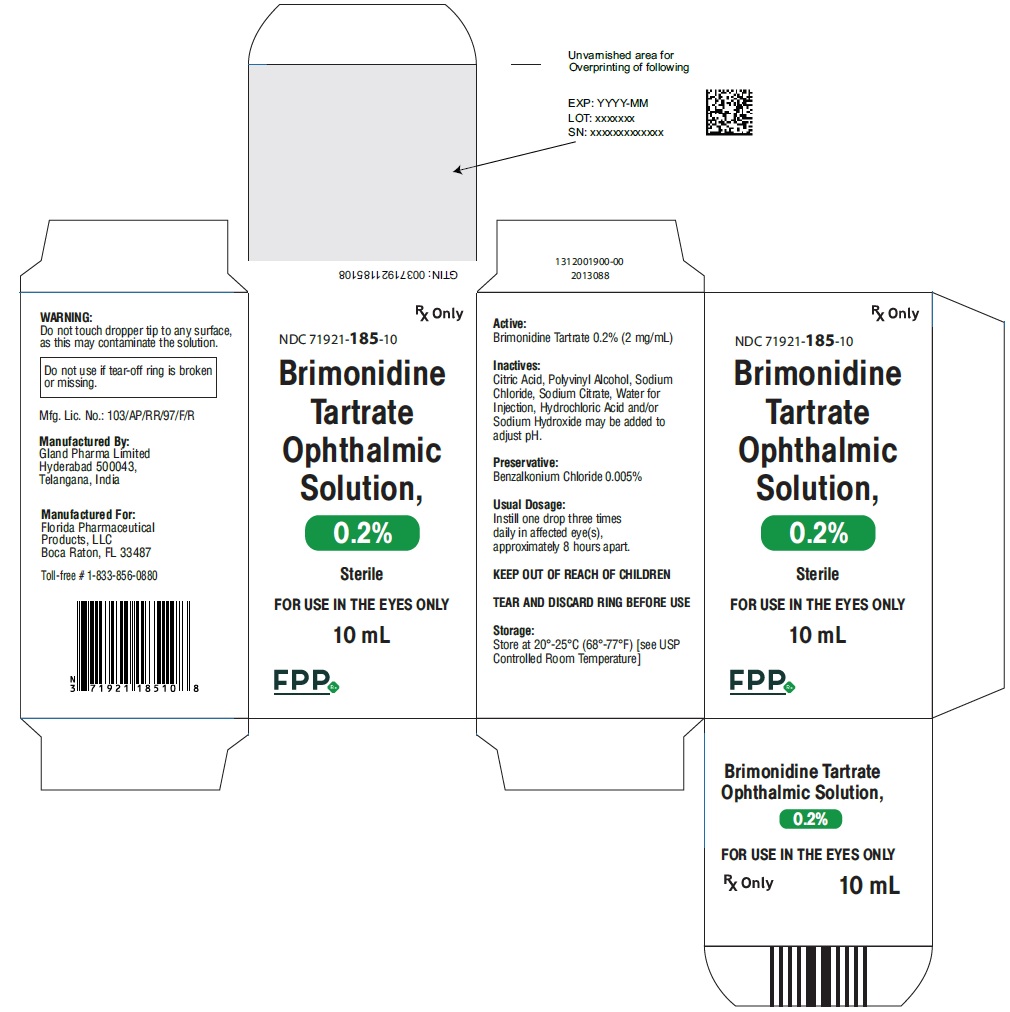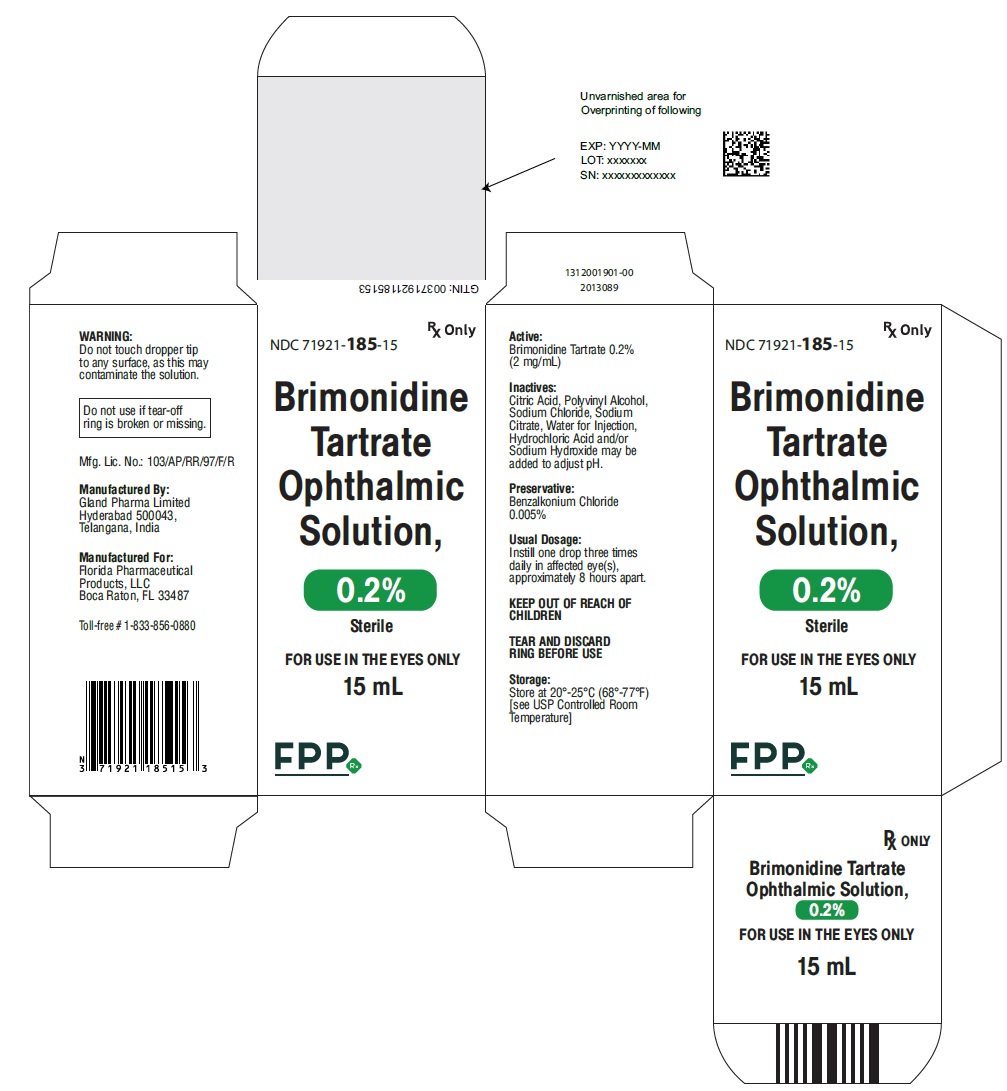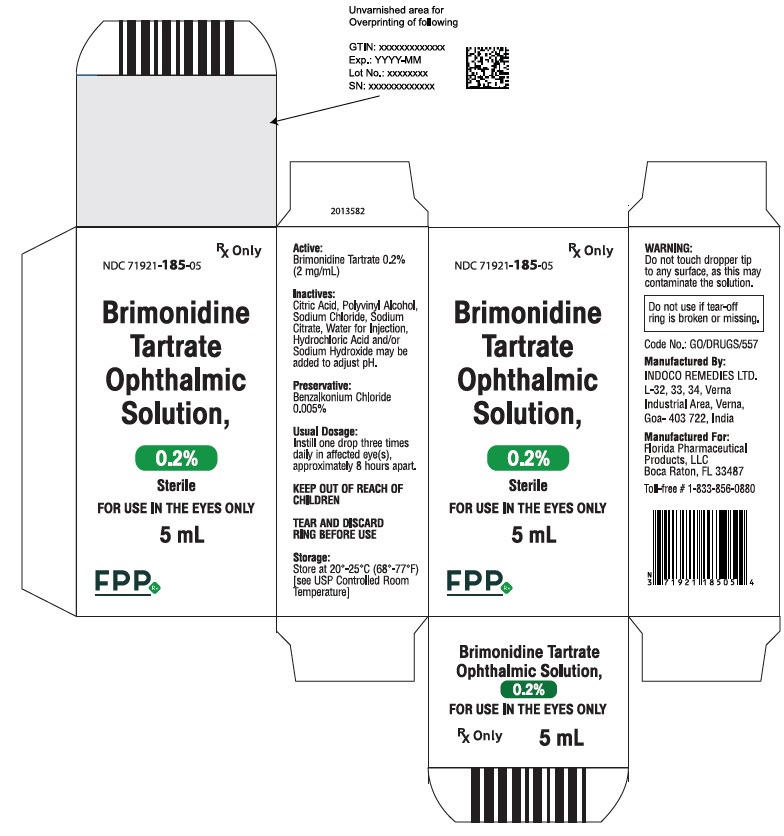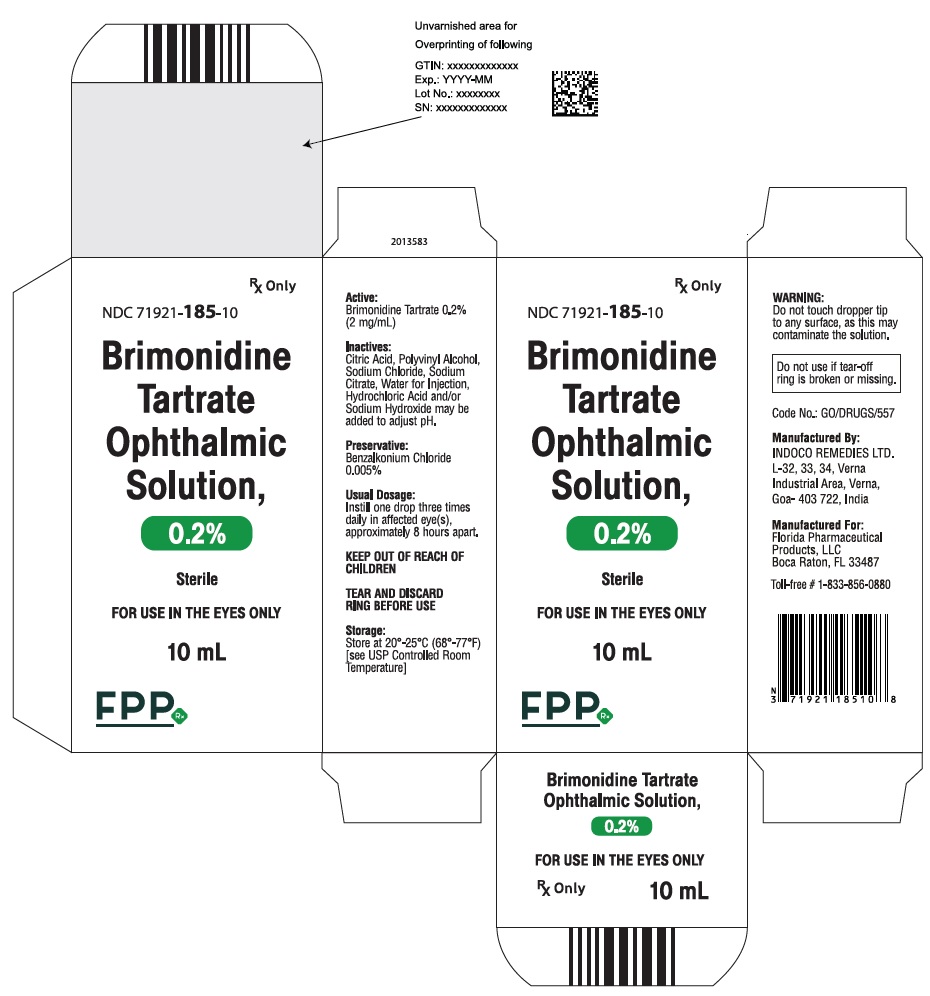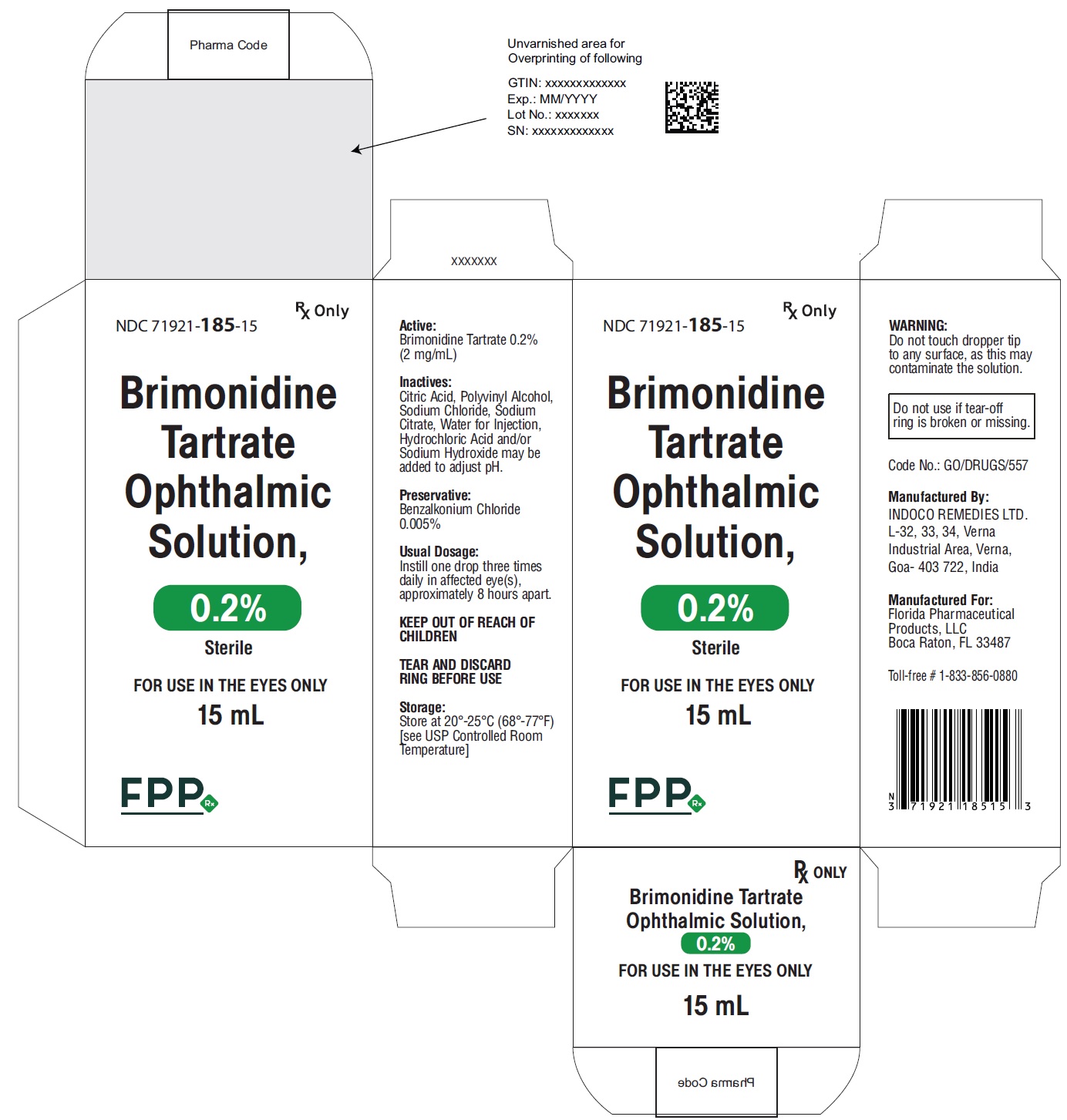 DRUG LABEL: Brimonidine Tartrate
NDC: 71921-185 | Form: SOLUTION/ DROPS
Manufacturer: Florida Pharmaceutical Products, LLC
Category: prescription | Type: Human Prescription Drug Label
Date: 20260128

ACTIVE INGREDIENTS: BRIMONIDINE TARTRATE 2 mg/1 mg
INACTIVE INGREDIENTS: Citric Acid Monohydrate; Polyvinyl Alcohol; Sodium Chloride; Sodium Citrate; Water; Hydrochloric acid; Sodium hydroxide; Benzalkonium Chloride

HIGHLIGHTS OF PRESCRIBING INFORMATION

These highlights do not include all the information needed to use BRIMONIDINE TARTRATE OPHTHALMIC SOLUTION, 0.2% safely and effectively. See full prescribing information for Brimonidine tartrate ophthalmic solution, 0.2% Brimonidine tartrate ophthalmic solution, 0.2%
For Topical Ophthalmic Use
Initial U.S. Approval: 1996

1 INDICATIONS & USAGE

Brimonidine Tartrate Ophthalmic Solution, 0.2% is an alpha adrenergic agonist indicated for lowering intraocular pressure (IOP) in patients with open-angle glaucoma or ocular hypertension. (1)

2 DOSAGE & ADMINISTRATION

One drop in the affected eye(s), three times daily, approximately 8 hours apart. (2)

3 DOSAGE FORMS & STRENGTHS

Solution containing 2 mg/mL brimonidine tartrate. (3)

4 CONTRAINDICATIONS

Neonates and infants (under the age of 2 years). (4.1)

5 WARNINGS AND PRECAUTIONS

Potentiation of vascular insufficiency. (5.1)

6 ADVERSE REACTIONS

Most common adverse reactions occurring in approximately 10 to 30% of patients receiving brimonidine tartrate ophthalmic solution 0.2% included oral dryness, ocular hyperemia, burning and stinging, headache, blurring, foreign body sensation, fatigue/drowsiness, conjunctival follicles, ocular allergic reactions, and ocular pruritus. (6.1)

To report SUSPECTED ADVERSE REACTIONS, contact at +1-833-856-0880 or FDA at 1-800-FDA-1088 or www.fda.gov/medwatch

7 DRUG INTERACTIONS

• Antihypertensives/cardiac glycosides may lower blood pressure. (7.1)
• Use with CNS depressants may result in an additive or potentiating effect. (7.2)
• Tricyclic antidepressants may potentially blunt the hypotensive effect of systemic clonidine. (7.3)
• Monoamine oxidase inhibitors may result in increased hypotension. (7.4)

8 USE IN SPECIFIC POPULATIONS

Use with caution in children > 2 years of age. (8.4)

FULL PRESCRIBING INFORMATION

1 INDICATIONS & USAGE

Brimonidine tartrate ophthalmic solution, 0.2% is indicated for lowering intraocular pressure in patients with open-angle glaucoma or ocular hypertension.

The IOP lowering efficacy of Brimonidine tartrate ophthalmic solution, 0.2% diminishes over time in some patients. This loss of effect appears with a variable time of onset in each patient and should be closely monitored.

2 DOSAGE & ADMINISTRATION

The recommended dose is one drop of Brimonidine tartrate ophthalmic solution, 0.2% in the affected eye(s) three times daily, approximately 8 hours apart.

Brimonidine tartrate ophthalmic solution, 0.2% may be used concomitantly with other topical ophthalmic drug products to lower intraocular pressure. If more than one topical ophthalmic product is being used, the products should be administered at least 5 minutes apart.

3 DOSAGE FORMS & STRENGTHS

Solution containing 2 mg/mL brimonidine tartrate.

4 CONTRAINDICATIONS

Brimonidine Tartrate Ophthalmic Solution, 0.2% is contraindicated in patients with hypersensitivity to brimonidine tartrate or any component of this medication. It is also contraindicated in patients receiving monoamine oxidase (MAO) inhibitor therapy.

4.1 Neonates and Infants (under the age of 2 years)

Brimonidine tartrate ophthalmic solution, 0.2% is contraindicated in neonates and infants (under the age of 2 years) [see Use in Specific Populations (8.4)].

4.2 Hypersensitivity Reactions

Brimonidine tartrate ophthalmic solution, 0.2% is contraindicated in patients who have exhibited a hypersensitivity reaction to any component of this medication in the past [see Adverse Reactions (6.1) and (6.2)].

5 WARNINGS AND PRECAUTIONS

5.1 Potentiation of Vascular Insufficiency

Brimonidine tartrate ophthalmic solution, 0.2% may potentiate syndromes associated with vascular insufficiency.

Brimonidine tartrate ophthalmic solution, 0.2% should be used with caution in patients with depression, cerebral or coronary insufficiency, Raynaud’s phenomenon, orthostatic hypotension, or thromboangiitis obliterans

5.2 Severe Cardiovascular Disease

Although brimonidine tartrate ophthalmic solution had minimal effect on the blood pressure of patients in clinical studies, caution should be exercised in treating patients with severe cardiovascular disease

5.3 Contamination of Topical Ophthalmic Products After Use

There have been reports of bacterial keratitis associated with the use of multiple-dose containers of topical ophthalmic products. These containers had been inadvertently contaminated by patients who, in most cases, had a concurrent corneal disease or a disruption of the ocular epithelial surface [see Patient Counseling Information (17)].

5.4 Use with Contact Lenses

The preservative in Brimonidine tartrate ophthalmic solution, 0.2%, benzalkonium chloride, may be absorbed by soft contact lenses. Patients wearing soft contact lenses should be instructed to wait at least 15 minutes after instilling Brimonidine Tartrate Ophthalmic Solution, 0.2% to insert soft contact lenses.

6 ADVERSE REACTIONS

The following serious adverse reactions are described elsewhere in the labeling:

- Potentiation of Vascular Insufficiency [see Warnings and Precautions (5.1)]
- Severe Cardiovascular Disease [see Warnings and Precautions (5.2)]
- Contamination of Topical Ophthalmic Products after Use [see Warnings and Precautions (5.3)]
- Neonates and Infants (under the age of 2 years) [see Contraindications (4.1)]

6.1 Clinical Studies Experience

Because clinical studies are conducted under widely varying conditions, adverse reaction rates observed in the clinical studies of a drug cannot be directly compared to rates in the clinical studies of another drug and may not reflect the rates observed in practice.

- Adverse reactions occurring in approximately 10 to 30% of the subjects (in descending order): oral dryness, ocular hyperemia, burning and stinging, headache, blurring, foreign body sensation, fatigue/drowsiness, conjunctival follicles, ocular allergic reactions, and ocular pruritus.
- Adverse reactions occurring in approximately 3 to 9% of the subjects (in descending order): corneal staining/erosion, photophobia, eyelid erythema, ocular ache/pain, ocular dryness, tearing, upper respiratory symptoms, eyelid edema, conjunctival edema, dizziness, blepharitis, ocular irritation, gastrointestinal symptoms, asthenia, conjunctival blanching, abnormal vision and muscular pain.
- Adverse reactions reported < 3% of the patients: lid crusting, conjunctival hemorrhage, abnormal taste, insomnia, conjunctival discharge, depression, hypertension, anxiety, palpitations/arrhythmias, nasal dryness and syncope.

6.2 Postmarketing Experience

The following reactions have been identified during postmarketing use of brimonidine tartrate ophthalmic solutions in clinical practice. Because they are reported voluntarily from a population of unknown size, estimates of frequency cannot be made. The reactions, which have been chosen
for inclusion due to either their seriousness, frequency of reporting, possible causal connection to brimonidine tartrate ophthalmic solutions, or a combination of these factors, include:
• Bradycardia; conjunctivitis; hypersensitivity; hypotension; iritis; keratoconjunctivitis sicca; lacrimation increased; miosis; nausea; skin reactions (including erythema, eyelid pruritus, rash, and vasodilation); and tachycardia.
• Apnea, bradycardia, coma, hypotension, hypothermia, hypotonia, lethargy, pallor, respiratory depression, and somnolence in infants receiving brimonidine tartrate ophthalmic solutions.

7 DRUG INTERACTIONS

7.1 Antihypertensive/Cardiac Glycosides

Because brimonidine tartrate ophthalmic solution, 0.2% may reduce blood pressure, caution in using drugs such as antihypertensives and/or cardiac glycosides with brimonidine tartrate ophthalmic solution, 0.2% is advised.

7.2 CNS Depressants

Although specific drug interaction studies have not been conducted with brimonidine tartrate ophthalmic solution, 0.2%, the possibility of an additive or potentiating effect with CNS depressants (alcohol, barbiturates, opiates, sedatives, or anesthetics) should be considered.

7.3 Tricyclic Antidepressants

Tricyclic antidepressants have been reported to blunt the hypotensive effect of systemic clonidine. It is not known whether the concurrent use of these agents with brimonidine tartrate ophthalmic solution, 0.2% in humans can lead to resulting interference with the IOP lowering effect. Caution is advised in patients taking tricyclic antidepressants which can affect the metabolism and uptake of circulating amines.

7.4 Monoamine Oxidase Inhibitors

Monoamine oxidase (MAO) inhibitors may theoretically interfere with the metabolism of brimonidine and potentially result in an increased systemic side-effect such as hypotension. Caution is advised in patients taking MAO inhibitors which can affect the metabolism and uptake of circulating amines.

8 USE IN SPECIFIC POPULATIONS

8.1 Pregnancy

Pregnancy Category B: Teratogenicity studies have been performed in animals.

Brimonidine tartrate was not teratogenic when given orally during gestation days 6 through 15 in rats and days 6 through 18 in rabbits. The highest doses of brimonidine tartrate in rats (2.5 mg/kg/day) and rabbits (5 mg/kg/day) achieved AUC exposure values 375-fold higher or 19-fold higher, respectively, than similar values estimated in humans treated with Brimonidine Tartrate Ophthalmic Solution, 0.2%, one drop in one eye, twice daily.

There are no adequate and well-controlled studies in pregnant women; however, in animal studies, brimonidine crossed the placenta and entered into the fetal circulation to a limited extent.
Because animal reproduction studies are not always predictive of human response, brimonidine tartrate ophthalmic solution, 0.2% should be used during pregnancy only if the potential benefit to the mother justifies the potential risk to the fetus.

8.3 Nursing Mothers

It is not known whether brimonidine tartrate is excreted in human milk, although in animal studies, brimonidine tartrate has been shown to be excreted in breast milk. Because of the potential for serious adverse reactions from brimonidine tartrate ophthalmic solution, 0.2% in nursing infants, a decision should be made whether to discontinue nursing or to discontinue the drug, taking into account the importance of the drug to the mother.

8.4 Pediatric Use

Brimonidine tartrate ophthalmic solution, 0.2% is contraindicated in children under the age of 2 years [see Contraindications (4.1)]. During postmarketing surveillance, apnea, bradycardia, coma, hypotension, hypothermia, hypotonia, lethargy, pallor, respiratory depression, and somnolence have been reported in infants receiving brimonidine. The safety and effectiveness of brimonidine tartrate have not been studied in children below the age of 2 years.

In a well-controlled clinical study conducted in pediatric glaucoma patients (ages 2 to 7 years) the most commonly observed adverse reactions with brimonidine tartrate ophthalmic solution, 0.2% dosed three times daily were somnolence (50 to 83% in patients ages 2 to 6 years) and decreased alertness. In pediatric patients 7 years of age (greater than 20 kg), somnolence appears to occur less frequently (25%). Approximately 16% of patients on brimonidine tartrate ophthalmic solution, 0.2% discontinued from the study due to somnolence.

8.5 Geriatric Use

No overall differences in safety or effectiveness have been observed between elderly and other adult patients.

8.6 Special Population

Brimonidine tartrate ophthalmic solution, 0.2% has not been studied in patients with hepatic impairment.

Brimonidine tartrate ophthalmic solution, 0.2% has not been studied in patients with renal impairment. The effect of dialysis on brimonidine pharmacokinetics in patients with renal failure is not known

10 OVERDOSAGE

Very limited information exists on accidental ingestion of brimonidine in adults; the only adverse reaction reported to date has been hypotension. Symptoms of brimonidine overdose have been reported in neonates, infants, and children receiving brimonidine tartrate as part of medical treatment of congenital glaucoma or by accidental oral ingestion [see Use In Specific Populations (8.4)]. Treatment of an oral overdose includes supportive and symptomatic therapy; a patent airway should be maintained.

11 DESCRIPTION

Brimonidine tartrate ophthalmic solution 0.2%, sterile, is a relatively selective alpha-2 adrenergic receptor agonist (topical intraocular pressure lowering agent).
The structural formula of brimonidine tartrate is:

5-Bromo-6-(2-imidazolidinylideneamino) quinoxaline L-tartrate; MW= 442.24

In solution, brimonidine tartrate ophthalmic solution 0.2% has a clear, greenish-yellow color. It has an osmolality of 280 to 330 mOsml/kg and a pH of 5.6 to 6.6.

Each mL of brimonidine tartrate ophthalmic solution 0.2% contains the active ingredient brimonidine tartrate 0.2% (2 mg/mL) with the inactive ingredients benzalkonium chloride 0.005% (0.05 mg/mL) as a preservative; citric acid; polyvinyl alcohol; sodium chloride; sodium citrate; and water for injection. Hydrochloric acid and/or sodium hydroxide may be added to adjust pH.

12 CLINICAL PHARMACOLOGY

12.1 Mechanism of Action

Brimonidine tartrate ophthalmic solution, 0.2% is a relatively selective alpha-2 adrenergic receptor agonist with a peak ocular hypotensive effect occurring at two hours post-dosing.

Fluorophotometric studies in animals and humans suggest that brimonidine tartrate has a dual mechanism of action by reducing aqueous humor production and increasing uveoscleral outflow.

12.3 Pharmacokinetics

Absorption
After ocular administration of a 0.2% solution, plasma concentrations peaked within 1 to 4 hours and declined with a systemic half-life of approximately 3 hours.

Distribution
The protein binding of brimonidine has not been studied.

Metabolism
In humans, brimonidine is extensively metabolized by the liver.
Excretion
Urinary excretion is the major route of elimination of brimonidine and its metabolites. Approximately 87% of an orally-administered radioactive dose of brimonidine was eliminated within 120 hours, with 74% found in the urine.

13 NONCLINICAL TOXICOLOGY

13.1 Carcinogenesis & Mutagenesis & Impairment Of Fertility

No compound-related carcinogenic effects were observed in either mice or rats following a 21 month and 24-month study, respectively. In these studies, dietary administration of brimonidine tartrate at doses up to 2.5 mg/kg/day in mice and 1.0 mg/kg/day in rats achieved ~77 and 118 times, respectively, the plasma Cmax drug concentration estimated in humans treated with one drop brimonidine tartrate ophthalmic solution 0.2% into both eyes 2 times per day.

Brimonidine tartrate was not mutagenic or clastogenic in a series of in vitro and in vivo studies including the Ames bacterial reversion test, chromosomal aberration assay in Chinese Hamster Ovary (CHO) cells, and three in vivo studies in CD-1 mice: a host-mediated assay, cytogenetic study, and dominant lethal assay.

A reproduction and fertility study in rats with brimonidine tartrate demonstrated no adverse effect on male or female fertility at oral doses up to 1 mg/kg, estimated as approximately 200 times the systemic exposure (AUC) following the maximum recommended human ophthalmic dose of brimonidine tartrate ophthalmic solution 0.5%.

14 CLINICAL STUDIES

Elevated IOP presents a major risk factor in glaucomatous field loss. The higher the level of IOP, the greater the likelihood of optic nerve damage and visual field loss. Brimonidine tartrate has the action of lowering intraocular pressure with minimal effect on cardiovascular and pulmonary parameters.

In comparative clinical studies with timolol 0.5%, lasting up to one year, the IOP lowering effect of Brimonidine tartrate ophthalmic solution, 0.2% was approximately 4 to 6 mm Hg compared with approximately 6 mm Hg for timolol. In these studies, both patient groups were dosed BID; however, due to the duration of action of Brimonidine tartrate ophthalmic solution, 0.2%, it is recommended that Brimonidine tartrate ophthalmic solution, 0.2% be dosed TID. Eight percent of subjects were discontinued from studies due to inadequately controlled intraocular pressure, which in 30% of these patients occurred during the first month of therapy. Approximately 20% were discontinued due to adverse experiences.

16 HOW SUPPLIED/STORAGE AND HANDLING

Brimonidine tartrate ophthalmic solution, 0.2% is supplied sterile, in white opaque LDPE plastic bottles and natural nozzle with purple tear-off HDPE caps as follows:

5 mL in 5mL bottle NDC 71921-185-05
10 mL in 10 mL bottle NDC 71921-185-10
15 mL in 15 mL bottle NDC 71921-185-15
STORAGE:
Store between 20°- 25°C (68°- 77°F) [See USP Controlled Room Temperature].
KEEP OUT OF THE REACH OF CHILDREN.
TEAR AND DISCARD RING BEFORE USE
Do not use if tear-off ring is broken or missing.

17 PATIENT COUNSELING INFORMATION

Handling the Container
Instruct patients that ocular solutions, if handled improperly or if the tip of the dispensing container contacts the eye or surrounding structures, can become contaminated by common bacteria known to cause ocular infections. Serious damage to the eye and subsequent loss of vision may result from using contaminated solutions [see Warnings and Precautions (5.3)]. Always replace the cap after using. If solution changes color or becomes cloudy, do not use. Do not use the product after the expiration date marked on the bottle.

When to Seek Physician Advice
Advise patients that if they have ocular surgery or develop an intercurrent ocular condition (e.g., trauma or infection), they should immediately seek their physician's advice concerning the continued use of the present multidose container.

Use with Contact Lenses
Advise patients that contact lenses should be removed prior to instillation of brimonidine tartrate ophthalmic solution 0.2% and may be reinserted 15 minutes following its administration.

Use with Other Ophthalmic Drugs
Advise patients that if more than one topical ophthalmic drug is being used, the drugs should be administered at least five minutes apart.

Potential for Decreased Mental Alertness
As with other similar medications, brimonidine tartrate ophthalmic solution 0.2% may cause fatigue and/or drowsiness in some patients. Caution patients who engage in hazardous activities of the potential for a decrease in mental alertness.

Manufactured for:

Florida Pharmaceutical Products, LLC

Boca Raton, FL, 33487

Toll-free # 1-833-856-0880

PACKAGE LABEL.PRINCIPAL DISPLAY PANEL

NDC 71921-185-05
Florida Pharmaceutical Products
Brimonidine Tartrate Ophthalmic Solution, 0.2%.
5ml in 5ml bottle Carton Label

NDC 71921-185-10
Florida Pharmaceutical Products
Brimonidine Tartrate Ophthalmic Solution, 0.2%.
10 ml in 10ml bottle Carton Label

NDC 71921-185-15
Florida Pharmaceutical Products
Brimonidine Tartrate Ophthalmic Solution, 0.2%.
10 ml in 10ml bottle Carton Label

Brimonidine Tartrate Ophthalmic Solution, 0.2%

5ml in 5ml bottle Carton Label

Brimonidine Tartrate Ophthalmic Solution, 0.2%
10 ml in 5ml bottle Carton Label

Brimonidine Tartrate Ophthalmic Solution, 0.2%
15 ml in 5ml bottle Carton Label